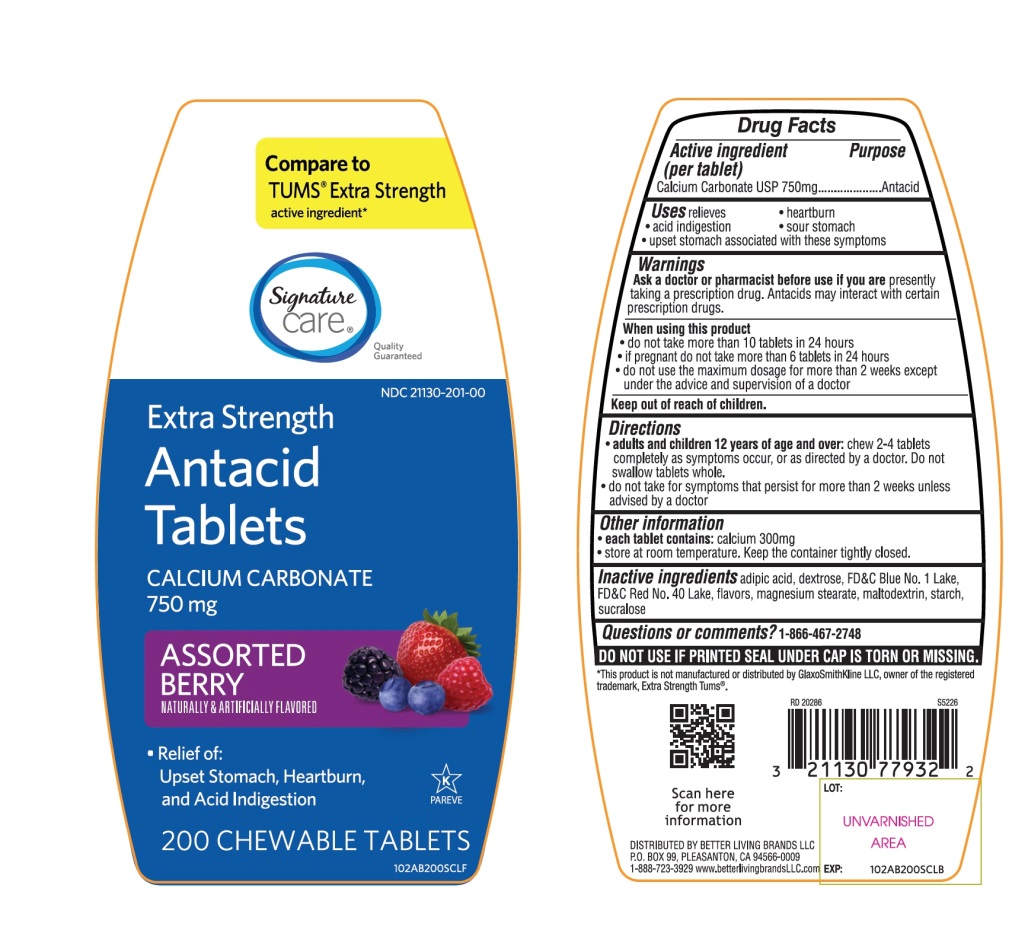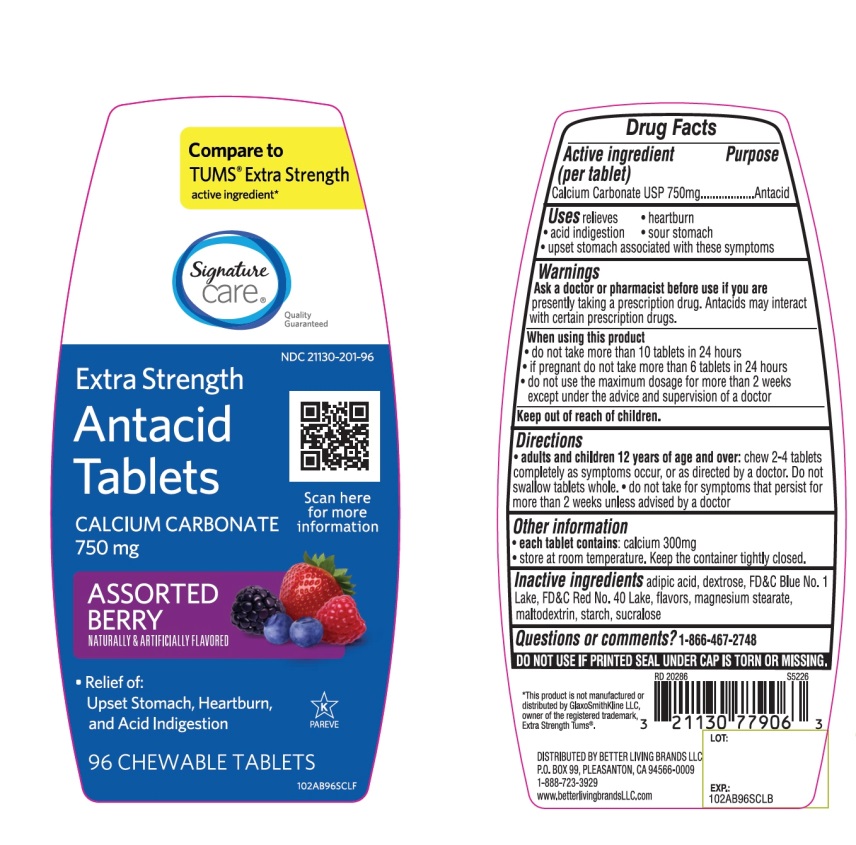 DRUG LABEL: Extra Strength
NDC: 21130-201 | Form: TABLET, CHEWABLE
Manufacturer: BETTER LIVING BRANDS, LLC
Category: otc | Type: HUMAN OTC DRUG LABEL
Date: 20251029

ACTIVE INGREDIENTS: CALCIUM CARBONATE 750 mg/1 1
INACTIVE INGREDIENTS: ADIPIC ACID; DEXTROSE, UNSPECIFIED FORM; FD&C BLUE NO. 1; FD&C RED NO. 40; MAGNESIUM STEARATE; MALTODEXTRIN; STARCH, CORN; SUCRALOSE

Extra Strength Antacid Calcium Drug Facts

Active ingredient (per tablet)

Calcium Carbonate USP 750mg

Purpose

Antacid

Uses

relieves

- heartburn
- acid indigestion
- sour stomach
- upset stomach associated with these symptoms

Warnings

Ask a doctor or pharmacist before use if you arepresently taking a prescription drug. Antacids may interact with certain prescription drugs.

When using this product

- do not take more than 10 tablets in 24 hours
- if pregnant do not take more than 6 tablets in 24 hours
- do not use the maximum dosage for more than 2 weeks except under the advice and supervision of a doctor.

Directions

- adults and children 12 years of age and over:chew 2-4 tablets completely as symptoms occur, or as directed by a doctor. Do not swallow tablets whole.
- do not take for symptoms that persist for more than 2 weeks unless advised by a doctor

Other information

- each tablet contains:elemental calcium 300mg
- store at room temperature. Keep the container tightly closed.
  Safety sealed: DO NOT USE IF PRINTED SEAL UNDER CAP IS TORN OR MISSING

Inactive ingredients

adipic acid, dextrose, FD&C Blue No. 1 Lake, FD&C Red No. 40 Lake, flavors, magnesium stearate, maltodextrin, starch, sucralose.

Questions?

1-866-467-2748

Package/Label Principal Display Panel

NDC # 21130-201-96

*Compare to active ingredient in Extra Strength Tums®

EXTRA STRENGTH

Antacid Tablets

Calcium Carbonate 750 mg

Fast Relief of Upset

Stomach, Heartburn & Acid Indigestion

Assorted Berries

Naturally & Artificially Flavored

96Chewable Tablets

GLUTEN- FREE

K PAREVE

Distributed by:

*This product is not manufactured or distributed by GlaxoSmithKline LLC, owner of the registered trademark, Extra Strength Tums®

Package Label for 96 Chewable Tablets